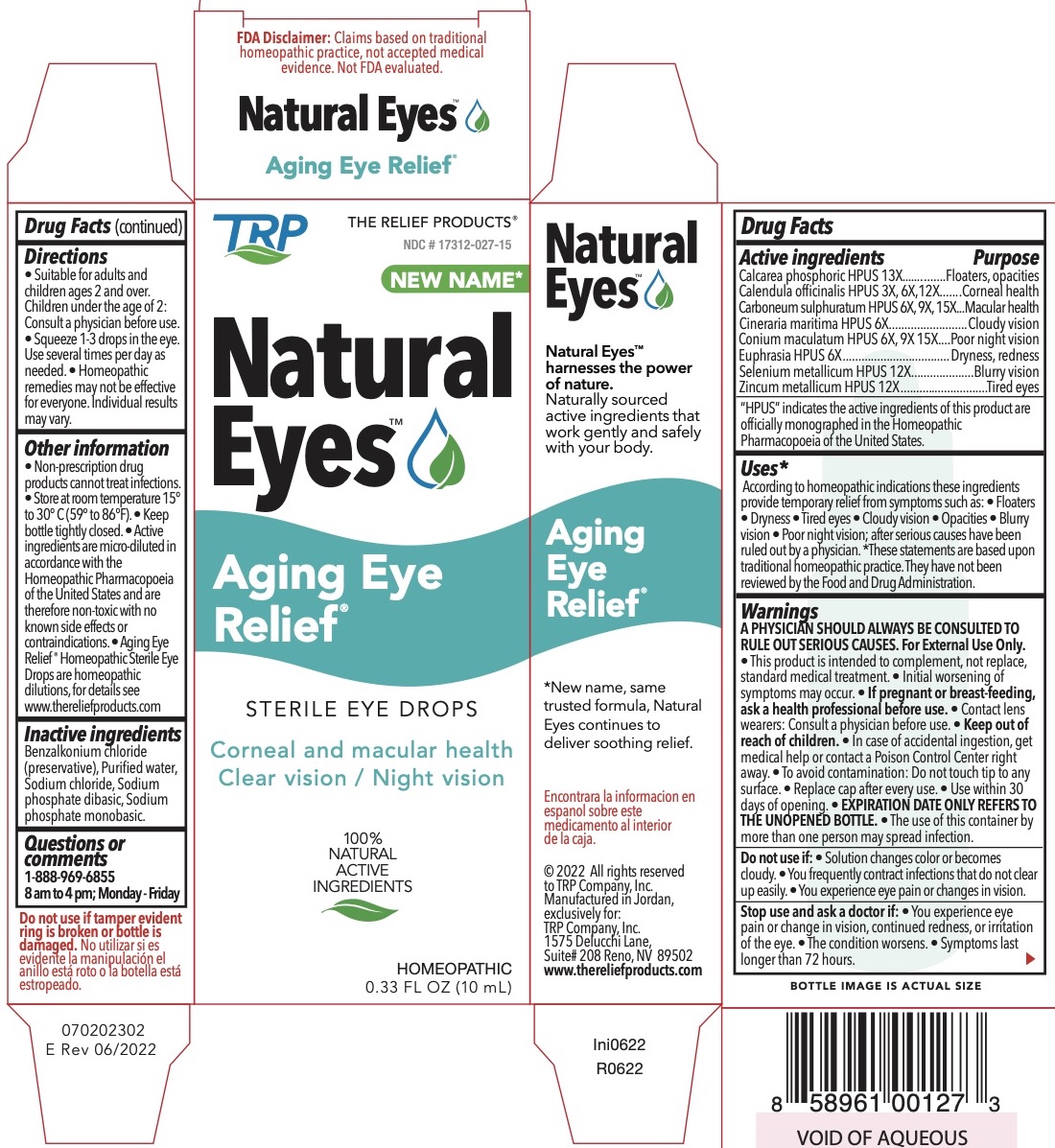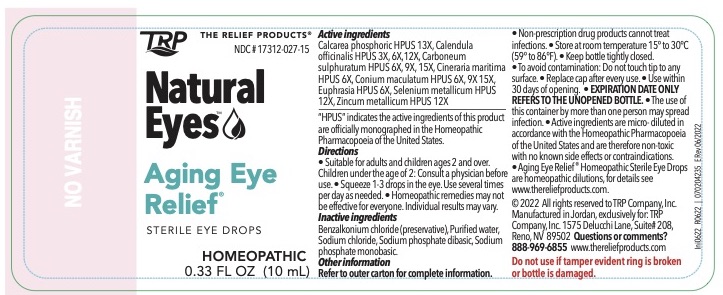 DRUG LABEL: AgingEye Relief
NDC: 17312-027 | Form: LIQUID
Manufacturer: TRP Company
Category: homeopathic | Type: HUMAN OTC DRUG LABEL
Date: 20230215

ACTIVE INGREDIENTS: TRIBASIC CALCIUM PHOSPHATE 13 [hp_X]/1 mL; CALENDULA OFFICINALIS FLOWERING TOP 3 [hp_X]/1 mL; CARBON DISULFIDE 6 [hp_X]/1 mL; JACOBAEA MARITIMA 5 [hp_X]/1 mL; CONIUM MACULATUM FLOWERING TOP 6 [hp_X]/1 mL; EUPHRASIA STRICTA 6 [hp_X]/1 mL; SELENIUM 12 [hp_X]/1 mL; ZINC 12 [hp_X]/1 mL
INACTIVE INGREDIENTS: BENZALKONIUM CHLORIDE; WATER; SODIUM CHLORIDE; SODIUM PHOSPHATE, DIBASIC; SODIUM PHOSPHATE, MONOBASIC

AgingEye Relief® Homeopathic Sterile Eye Drops

Active Ingredients | Purpose
Calcarea phosphorica HPUS 13x | Floaters, Opacities
Calendula officinalis (marigold containing lutein) HPUS 3x, 6x,12x | Corneal health
Carboneum sulphuratum HPUS 6x, 9x, 15x | Macular health
Cineraria maritima HPUS 5x | Cloudy vision
Conium maculatum HPUS 6x, 9x 15x | Poor night vision
Euphrasia HPUS 6x | Dryness, Redness
Selenium metallicum HPUS 12x | Blurry vision
Zincum metallicum HPUS 12x | Tired eyes

"HPUS" indicates the active ingredients are in the Homeopathic Pharmacopoeia of the United States.

Uses:*
According to homeopathic indications these ingredients provide temporary relief from symptoms such as:
• floaters • dryness • tired eyes • cloudy vision • opacities • blurry vision • Poor night vision; after serious causes have been ruled out by a physician..
*These statements are based upon traditional homeopathic practice. They have not been reviewed by the Food and Drug Administration.

Warnings:
A PHYSICIAN SHOULD ALWAYS BE CONSULTED TO RULE OUT SERIOUS CAUSES.
For External Use Only.

- This product is intended to complement not replace, standard medical treatment.
- Initial worsening of symptoms may occur.

PREGNANCY OR BREAST FEEDING

- If pregnant or breast-feeding, ask a health professional before use.

WARNINGS

- Contact lens wearers consult physician before use.
- To avoid contamination - do not touch tip to any surface.
- Replace cap after every use.
- Use within 30 days of opening.
- EXPIRATION DATE ONLY REFERS TO THE UNOPENED BOTTLE.
- The use of this container by more than one person may spread infection.

Do not use:

- If solution changes color or becomes cloudy.
- If you frequently contract infections that do not clear up easily.
- If you experience eye pain or changes in vision.

Stop use and ask a doctor if:

- You experience eye pain, changes in vision, continued redness or irritation of the eye.
- The condition worsens.
- Symptoms last longer than 72 hours.

Keep out of reach of children

• In case of accidental ingestion, get medical help or contact a Poison Control Center right away.

Directions:
• Suitable for adults and children ages 2 and over. Children under the age of 2: Consult a physician before use. Squeeze 1-3 drops in the eye. Use several times per day as needed. Homeopathic remedies may not be effective for everyone. Individual results may vary.

Other information:

- Non-prescription drug products cannot treat infections. • Store at room temperature 15° to 30° C (59° to 86°F) • Keep bottle tightly closed. • Active ingredients are micro-diluted in accordance with the Homeopathic Pharmacopoeia of the United States and are therefore non-toxic with no known side effects or contraindications. AgingEye Relief® Homeopathic Sterile Eye Drops are homeopathic dilutions, for details see www.thereliefproducts.com.

Inactive Ingredients:
Benzalkonium Chloride (preservative), Purified water, Sodium Chloride, Sodium Phosphate DiBasic, Sodium Phosphate Monobasic

Questions or comments?

www.thereliefproducts.com, 1-888-969-6855